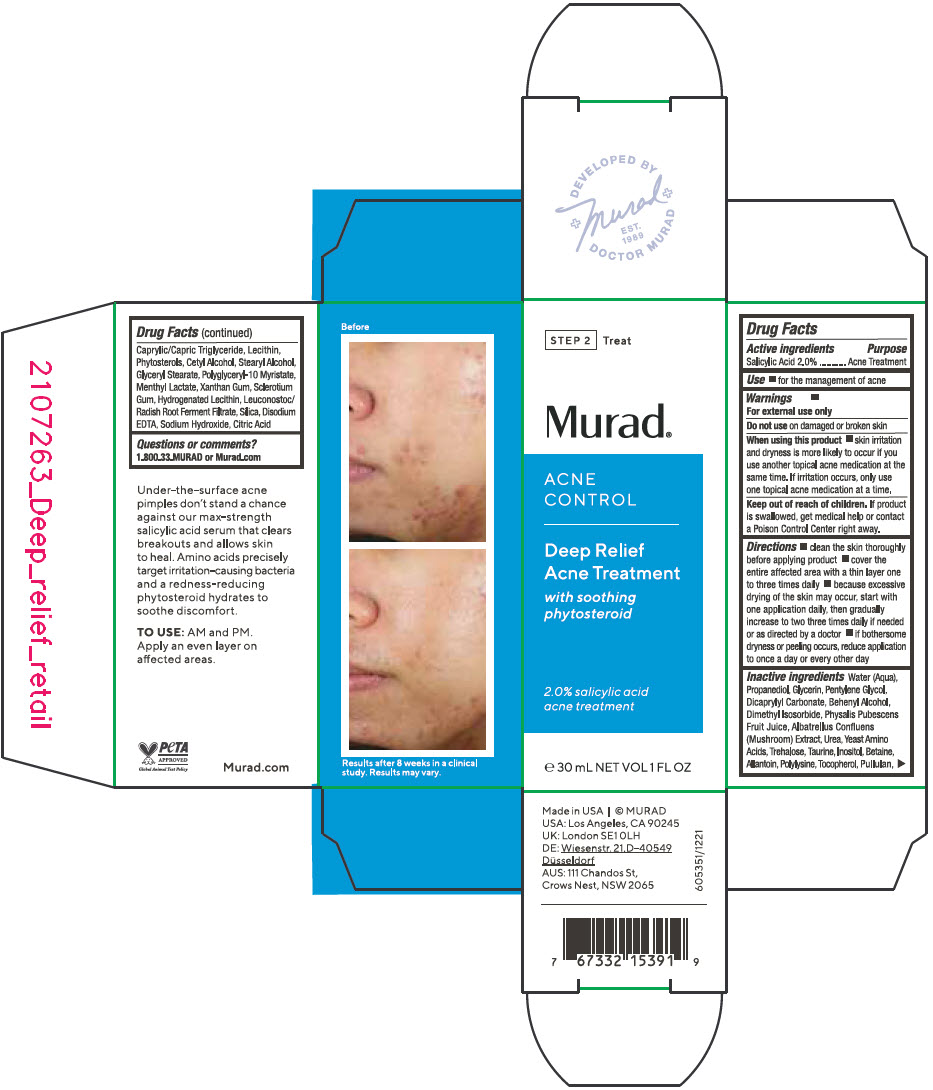 DRUG LABEL: Deep Relief Acne (Blemish) Treatment
NDC: 70381-121 | Form: SOLUTION
Manufacturer: Murad, LLC
Category: otc | Type: HUMAN OTC DRUG LABEL
Date: 20220223

ACTIVE INGREDIENTS: SALICYLIC ACID 2 g/100 mL
INACTIVE INGREDIENTS: WATER; PROPANEDIOL; GLYCERIN; PENTYLENE GLYCOL; DICAPRYLYL CARBONATE; DOCOSANOL; DIMETHYL ISOSORBIDE; PHYSALIS PUBESCENS FRUIT JUICE; ALBATRELLUS CONFLUENS FRUITING BODY; UREA; AMINO ACIDS, SOURCE UNSPECIFIED; TREHALOSE; INOSITOL; TAURINE; BETAINE; ALLANTOIN; POLY-L-LYSINE (30000-70000 MW); TOCOPHEROL; PULLULAN; MEDIUM-CHAIN TRIGLYCERIDES; LECITHIN, SOYBEAN; CETYL ALCOHOL; STEARYL ALCOHOL; GLYCERYL MONOSTEARATE; MENTHYL LACTATE, (-)-; XANTHAN GUM; BETASIZOFIRAN; HYDROGENATED SOYBEAN LECITHIN; LEUCONOSTOC/RADISH ROOT FERMENT FILTRATE; SILICON DIOXIDE; EDETATE DISODIUM ANHYDROUS; SODIUM HYDROXIDE; CITRIC ACID MONOHYDRATE; POLYGLYCERYL-10 MYRISTATE; RAPESEED STEROL; SOY STEROL

Deep Relief Acne (Blemish) Treatment

Drug Facts

Active ingredients

Salicylic Acid 2.0%

Purpose

Acne Treatment

Use

- for the management of acne

Warnings

For external use only

Do not use on damaged or broken skin

When using this product

- skin irritation and dryness is more likely to occur if you use another topical acne medication at the same time. If irritation occurs, only use one topical acne medication at a time.

Keep out of reach of children. If product is swallowed, get medical help or contact a Poison Control Center right away.

Directions

- clean the skin thoroughly before applying product
- cover the entire affected area with a thin layer one to three times daily
- because excessive drying of the skin may occur, start with one application daily, then gradually increase to two three times daily if needed or as directed by a doctor
- if bothersome dryness or peeling occurs, reduce application to once a day or every other day

Inactive ingredients

Water (Aqua), Propanediol, Glycerin, Pentylene Glycol, Dicaprylyl Carbonate, Behenyl Alcohol, Dimethyl Isosorbide, Physalis Pubescens Fruit Juice, Albatrellus Confluens (Mushroom) Extract, Urea, Yeast Amino Acids, Trehalose, Taurine, Inositol, Betaine, Allantoin, Polylysine, Tocopherol, Pullulan, Caprylic/Capric Triglyceride, Lecithin, Phytosterols, Cetyl Alcohol, Stearyl Alcohol, Glyceryl Stearate, Polyglyceryl-10 Myristate, Menthyl Lactate, Xanthan Gum, Sclerotium Gum, Hydrogenated Lecithin, Leuconostoc/Radish Root Ferment Filtrate, Silica, Disodium EDTA, Sodium Hydroxide, Citric Acid

Questions or comments?

1.800.33.MURAD or Murad.com

PRINCIPAL DISPLAY PANEL - 30 mL Bottle Carton

STEP 2
Treat

Murad®

ACNE
CONTROL

Deep Relief
Acne Treatment

with soothing
phytosteroid

2.0% salicylic acid
acne treatment

℮ 30 mL NET VOL 1 FL OZ